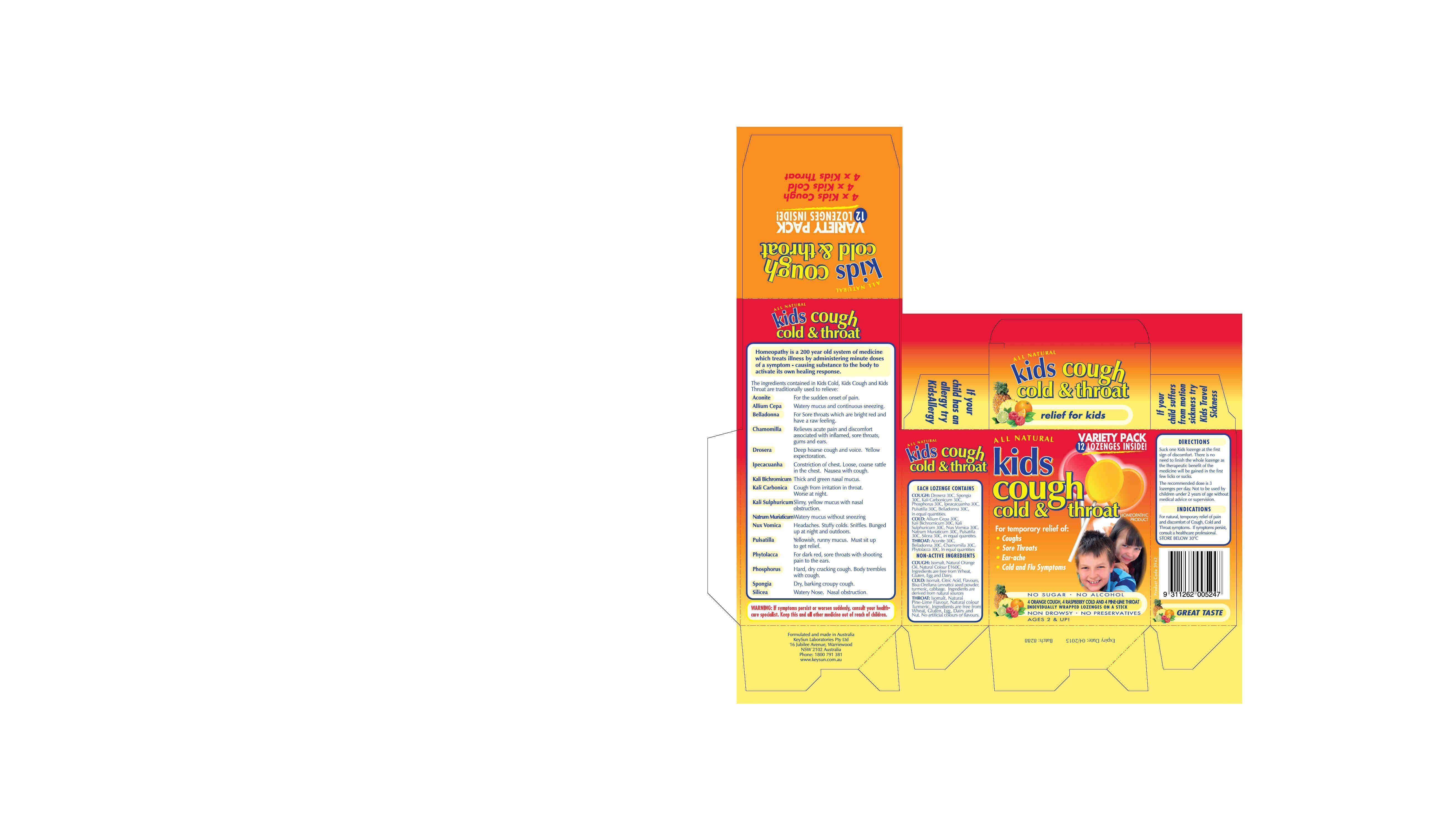 DRUG LABEL: kids cough cold and throat
                
NDC: 76509-400 | Form: KIT | Route: ORAL
Manufacturer: Natures Investment Holdings Pty Ltd dba Maxrelief USA
Category: homeopathic | Type: HUMAN OTC DRUG LABEL
Date: 20140531

ACTIVE INGREDIENTS: DROSERA INTERMEDIA 30 [hp_X]/1 1; SPONGIA OFFICINALIS WHOLE 30 [hp_X]/1 1; POTASSIUM CARBONATE 30 [hp_X]/1 1; PHOSPHORUS 30 [hp_X]/1 1; PULSATILLA VULGARIS 30 [hp_X]/1 1; ATROPA BELLADONNA 30 [hp_X]/1 1; IPECAC 30 [hp_X]/1 1; ONION 30 [hp_X]/1 1; POTASSIUM DICHROMATE 30 [hp_X]/1 1; POTASSIUM SULFATE 30 [hp_X]/1 1; STRYCHNOS NUX-VOMICA SEED 30 [hp_X]/1 1; SODIUM CHLORIDE 30 [hp_X]/1 1; PULSATILLA VULGARIS 30 [hp_X]/1 1; SILICON DIOXIDE 30 [hp_X]/1 1; ACONITUM NAPELLUS 30 [hp_X]/1 1; BELLADONNA LEAF 30 [hp_X]/1 1; MATRICARIA RECUTITA 30 [hp_X]/1 1; PHYTOLACCA AMERICANA ROOT 30 [hp_X]/1 1
INACTIVE INGREDIENTS: ISOMALT; SORBITOL; CITRIC ACID MONOHYDRATE; BIXA ORELLANA SEED; TURMERIC; CABBAGE; ISOMALT

Homeopathic Drug Facts

INACTIVE INGREDIENT

Non-Active Ingredients for Cough:

Isomalt, Natural Orange Oil, Natural Colour E160C

Non-Active Ingredients for Cold:

Isomalt, Citric Acid, Flavours,

Bixa Orellana (annatto) seed powder,

turmeric, cabbage.

Non-Active Ingredients for Throat:

Isomalt, Natural Pine-Lime Flavour,

Natural Colour, Turmeric.

Active Ingredients

Each Lozenge Contains for kids cough:

Drosera 30C, Spongia 30C, Kali Carbonicum 30C,

Phospherous 30C, Ipeacacuanha 30C,

Pulsatilla 30C, Belladonna 30C

in equal quantities

Each Lozenge Contains for kids cold:

Alium Cepa 30C, Kali Bichromicum 30C,

Kali Sulphuricum 30C, Nux Vomica 30C,

Natrum Muriaticum 30C, Pulsatilla

30C, Silcea 30C, in equal quantities.

Each Lozenge contains for kids throat:

Aconite 30C, Belladonna 30C, Chamomilla

30C, Phytolacca 30C, in equal quantities.

PURPOSE

Indications for kids cough:

For natural, temporary relief of pain and

discomfort of Cough, Cold and Throat symptoms.

Indications for kids cold:

For natural, temporary relief of pain and

discomfort of Cough, Cold and Throat symptoms.

Indications for kids throat:

For natural, temporary relief of pain and

discomfort of Cough, Cold and Throat symptoms.

WARNINGS

Warning for kids cough:

Warning: If symptoms persist or worsen suddenly, consult your health-

care specialist. Keep this and all other medicine out of reach of children.

Warning for kids cold:

Warning: If symptoms persist or worsen suddenly, consult your health-

care specialist. Keep this and all other medicine out of reach of children.

Warning for kids throat:

Warning: If symptoms persist or worsen suddenly, consult your health-

care specialist. Keep this and all other medicine out of reach of children.

Keep Out of Reach of Children for kids cough:

Keep this and all other medicine out of reach of children.

Keep Out of Reach of Children for kids cold:

Keep this and all other medicine out of reach of children.

Keep Out of Reach of Children for kids throat:

Keep this and all other medicine out of reach of children.

DOSAGE AND ADMINISTRATION

Directions for kids cough:

Suck one Kids lozenge at the first

sign of discomfort. There is no need to finish the whole

lozenge as the therapeutic benefit of the medicine will be

gained in the first few licks or sucks.

The recommended dose is 3 lozenges per day. Not to be

used by children under 2 years of age without medical advice

or supervision.

Directions for kids cold:

Suck one Kids lozenge at the first

sign of discomfort. There is no need to finish the whole

lozenge as the therapeutic benefit of the medicine will be

gained in the first few licks or sucks.

The recommended dose is 3 lozenges per day. Not to be

used by children under 2 years of age without medical advice

or supervision.

Directions for kids throat:

Suck one Kids lozenge at the first

sign of discomfort. There is no need to finish the whole

lozenge as the therapeutic benefit of the medicine will be

gained in the first few licks or sucks.

The recommended dose is 3 lozenges per day. Not to be used

by children under 2 years of age without medical advice or

supervision.

Indications for kids cough:

For natural, temporary relief of pain and

discomfort of Cough, Cold and Throat symptoms.

Indications for kids cold:

For natural, temporary relief of pain and

discomfort of Cough, Cold and Throat symptoms.

Indications for kids throat:

For natural, temporary relief of pain and

discomfort of Cough, Cold and Throat symptoms.

Storage for kids cough:

STORE BELOW 30 C

Storage for kids cold:

STORE BELOW 30 C

Storage for kids throat:

STORE BELOW 30 C